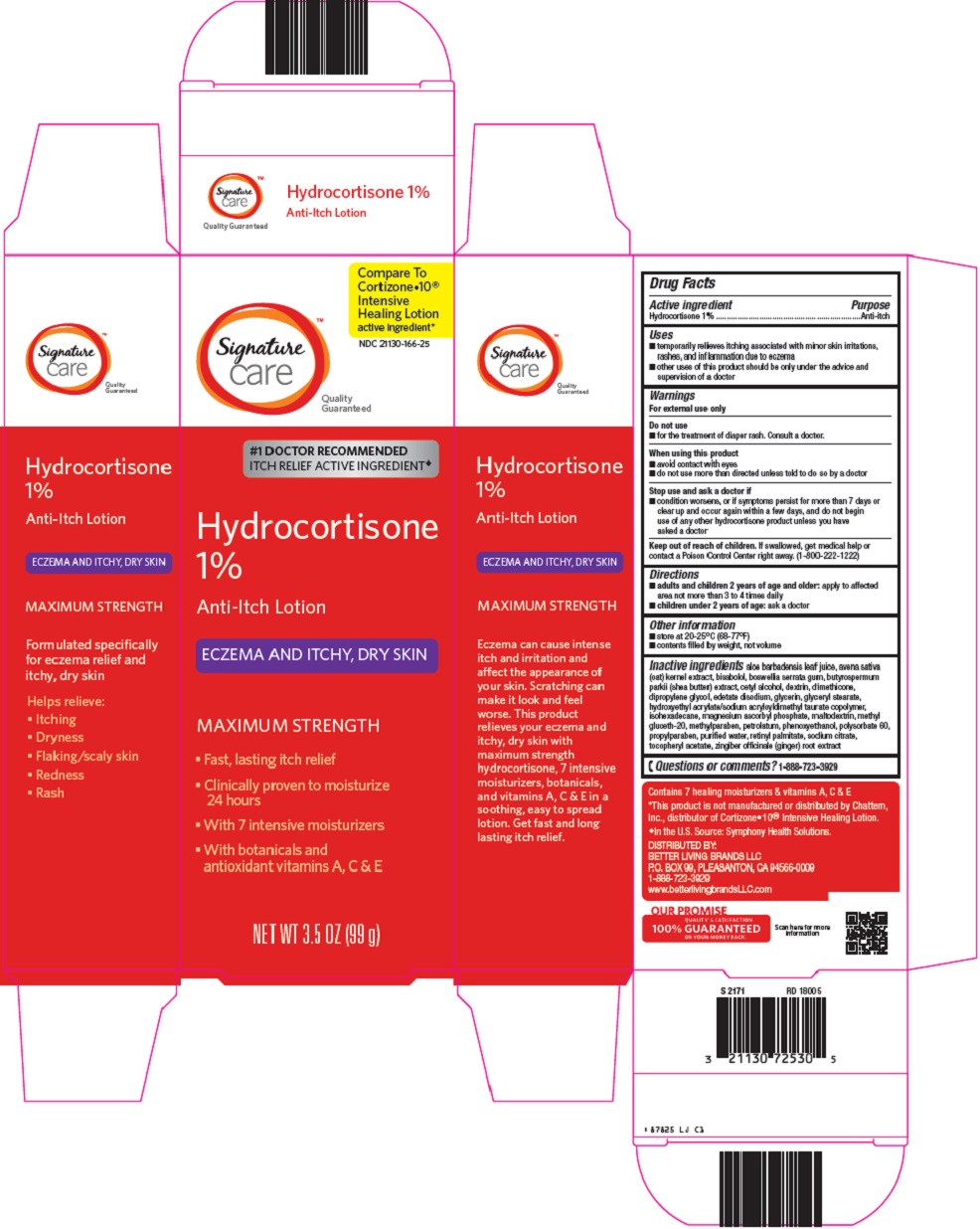 DRUG LABEL: signature care Hydrocortisone
NDC: 21130-166 | Form: LOTION
Manufacturer: Safeway
Category: otc | Type: HUMAN OTC DRUG LABEL
Date: 20250206

ACTIVE INGREDIENTS: HYDROCORTISONE 1 g/100 g
INACTIVE INGREDIENTS: ALOE VERA LEAF; OAT; LEVOMENOL; INDIAN FRANKINCENSE; SHEA BUTTER; CETYL ALCOHOL; DIMETHICONE; DIPROPYLENE GLYCOL; EDETATE DISODIUM; GLYCERIN; GLYCERYL MONOSTEARATE; ISOHEXADECANE; MAGNESIUM ASCORBYL PHOSPHATE; MALTODEXTRIN; METHYL GLUCETH-20; METHYLPARABEN; PETROLATUM; PHENOXYETHANOL; POLYSORBATE 60; PROPYLPARABEN; WATER; VITAMIN A PALMITATE; SODIUM CITRATE, UNSPECIFIED FORM; .ALPHA.-TOCOPHEROL ACETATE; GINGER

Better Living Brands LLC Hydrocortisone 1% Drug Facts

Active ingredient

Hydrocortisone 1%

Purpose

Anti-itch

Uses

- temporarily relieves itching associated with minor skin irritations, rashes, and inflammation due to eczema
- other uses of this product should be only under the advice and supervision of a doctor

Warnings

For external use only

Do not use

- for the treatment of diaper rash. Consult a doctor.

When using this product

- avoid contact with eyes
- do not use more than directed unless told to do so by a doctor

Stop use and ask a doctor if

- condition worsens, or if symptoms persist for more than 7 days or clear up and occur again within a few days, and do not begin use of any other hydrocortisone product unless you have asked a doctor

Keep out of reach of children.

If swallowed, get medical help or contact a Poison Control Center right away. (1-800-222-1222)

Directions

- adults and children 2 years of age and older: apply to affected area not more than 3 to 4 times daily
- children under 2 years of age: ask a doctor

Other information

- store at 20-25°C (68-77°F)
- contents filled by weight, not volume

Inactive ingredients

aloe barbadensis leaf juice, avena sativa (oat) kernel extract, bisabolol, boswellia serrata gum, butyrospermum parkii (shea butter) extract, cetyl alcohol, dextrin, dimethicone, dipropylene glycol, edetate disodium, glycerin, glyceryl stearate, hydroxyethyl acrylate/sodium acryloyldimethyl taurate copolymer, isohexadecane, magnesium ascorbyl phosphate, maltodextrin, methyl gluceth-20, methylparaben, petrolatum, phenoxyethanol, polysorbate 60, propylparaben, purified water, retinyl palmitate, sodium citrate, tocopheryl acetate, zingiber officinale (ginger) root extract

Questions or comments?

1-888-723-3929

Package/Label Principal Display Panel

Compare To Cortizone●10® Intensive Healing Lotion active ingredient

Quality Guaranteed

#1 DOCTOR RECOMMENDED ITCH RELIEF ACTIVE INGREDIENT

Hydrocortisone 1%

Anti-Itch Lotion

ECZEMA AND ITCHY, DRY SKIN

MAXIMUM STRENGTH

Fast, lasting itch relief

Clinically proven to moisturize 24 hours

With 7 intensive moisturizers

With botanicals and antioxidant vitamins A, C & E

NET WT 3.5 OZ (99 g)